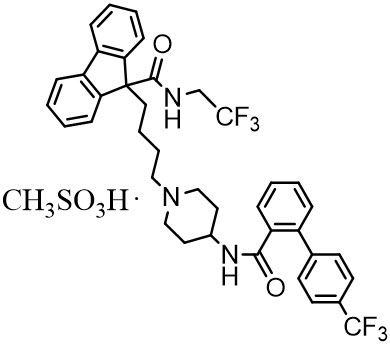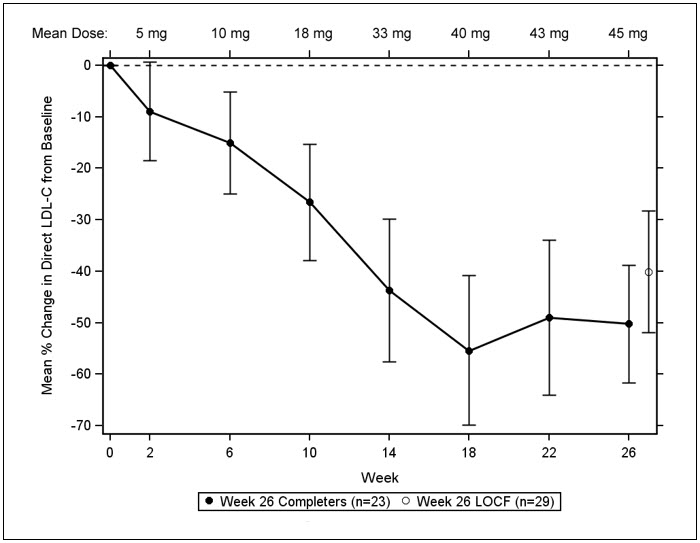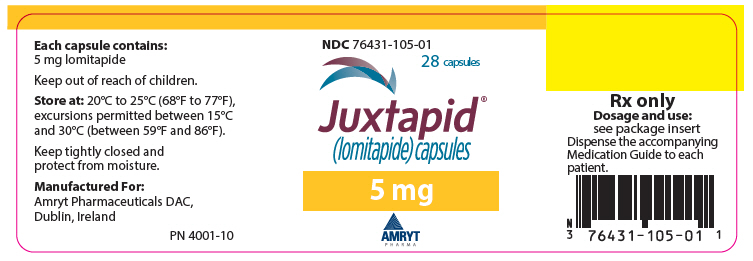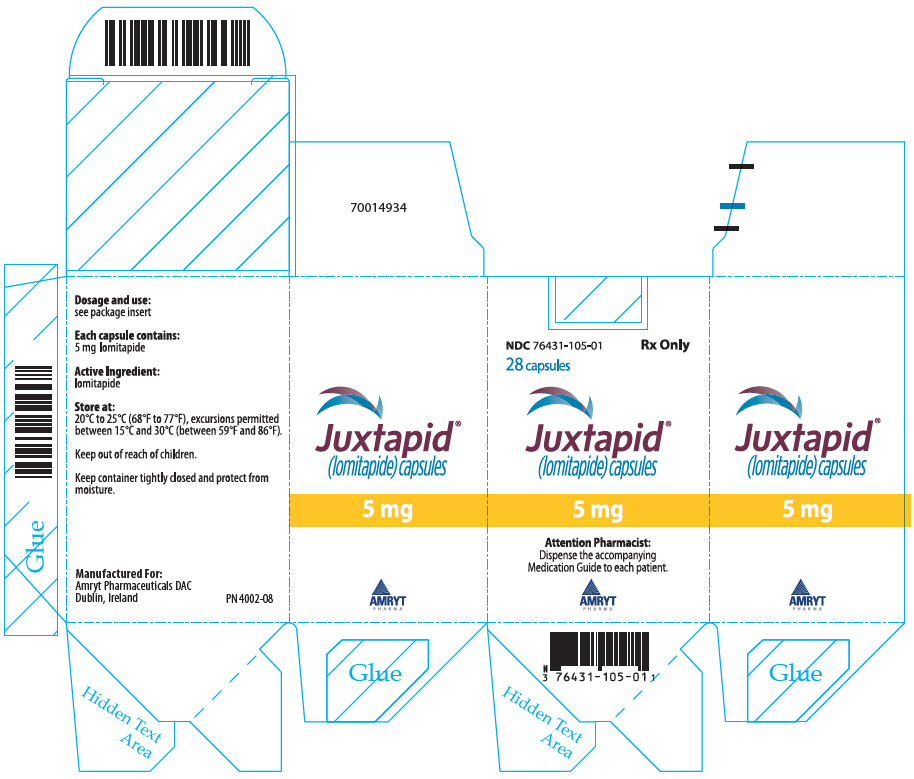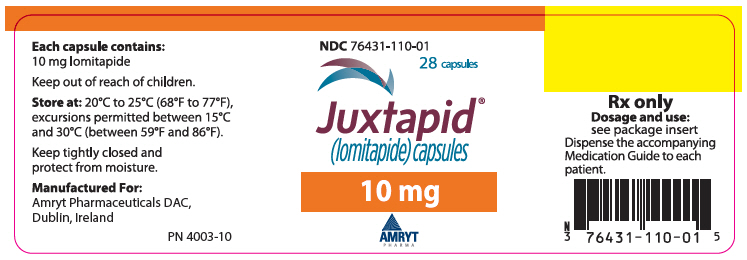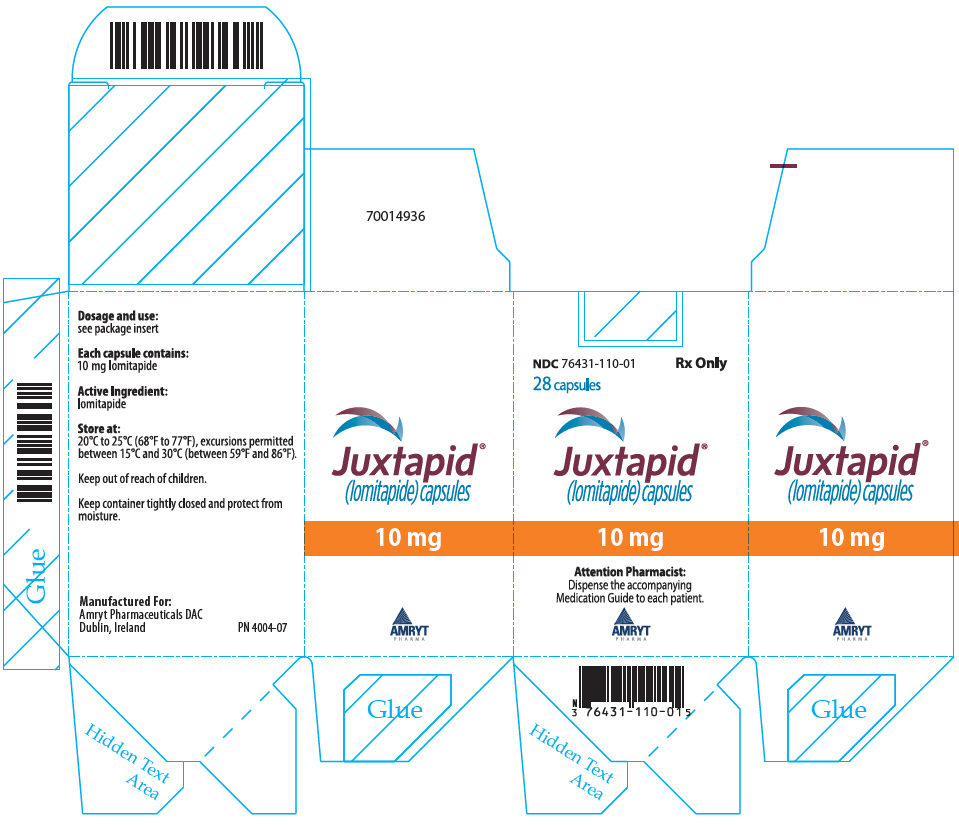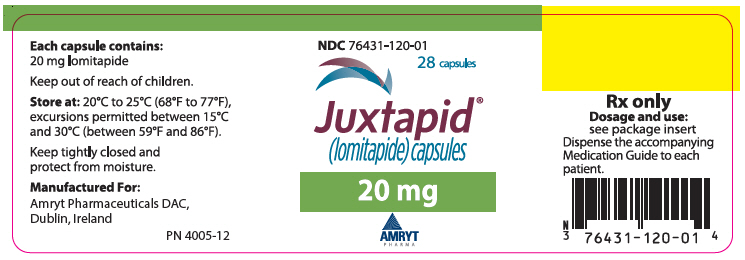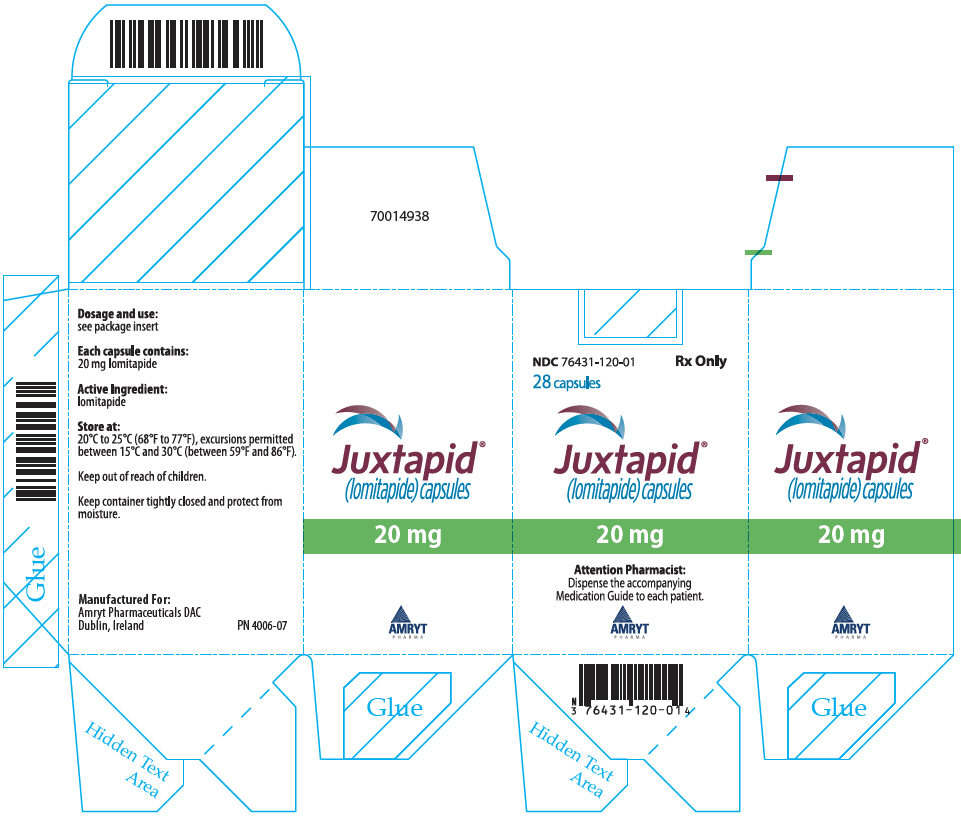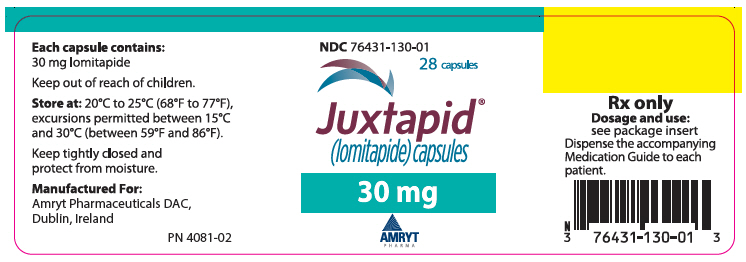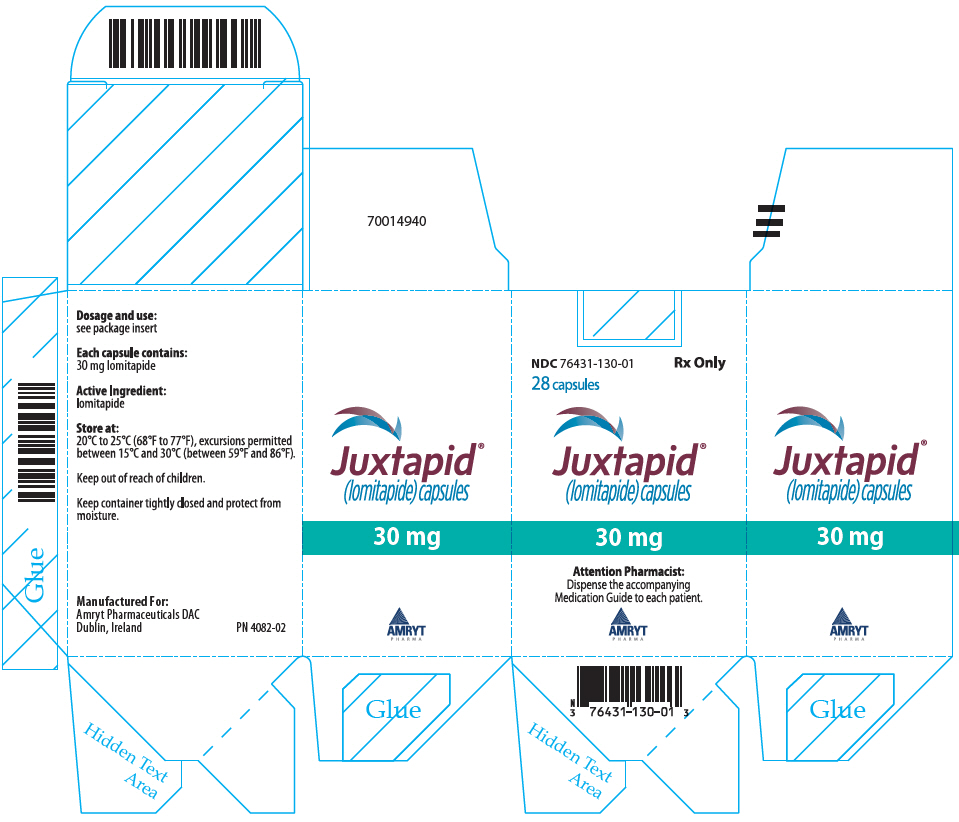 DRUG LABEL: Juxtapid
NDC: 76431-105 | Form: CAPSULE
Manufacturer: Amryt Pharmaceuticals DAC
Category: prescription | Type: HUMAN PRESCRIPTION DRUG LABEL
Date: 20260120

ACTIVE INGREDIENTS: LOMITAPIDE MESYLATE 5 mg/1 1

HIGHLIGHTS OF PRESCRIBING INFORMATION

These highlights do not include all the information needed to use JUXTAPID safely and effectively. See full prescribing information for JUXTAPID.
JUXTAPID® (lomitapide) capsules, for oral use
Initial U.S. Approval: 2012

WARNING: RISK OF HEPATOTOXICITY

See full prescribing information for complete boxed warning.

JUXTAPID can cause elevations in transaminases (5.1).

- Measure alanine and aspartate aminotransferases (ALT, AST), alkaline phosphatase, and total bilirubin before initiating treatment and then ALT and AST regularly as recommended (2.4, 5.1).
- During treatment, adjust the dose of JUXTAPID if the ALT or AST is ≥3 times the upper limit of normal (ULN) (2.4, 5.1).
- Discontinue JUXTAPID for clinically significant liver toxicity (2.4, 5.1).

JUXTAPID increases hepatic fat (hepatic steatosis) with or without concomitant increases in transaminases (5.1).

- Hepatic steatosis associated with JUXTAPID may be a risk factor for progressive liver disease, including steatohepatitis and cirrhosis (5.1).

Because of the risk of hepatotoxicity, JUXTAPID is available only through a restricted program called the JUXTAPID REMS Program (5.2). Prescribe JUXTAPID only to patients with a clinical or laboratory diagnosis consistent with HoFH. The safety and effectiveness of JUXTAPID have not been established in patients with hypercholesterolemia who do not have HoFH (1).

1 INDICATIONS AND USAGE

JUXTAPID is a microsomal triglyceride transfer protein inhibitor indicated as an adjunct to a low-fat diet and other lipid-lowering treatments, including LDL apheresis where available, to reduce low-density lipoprotein cholesterol (LDL-C), total cholesterol (TC), apolipoprotein B (apo B), and non-high-density lipoprotein cholesterol (non-HDL-C) in patients with homozygous familial hypercholesterolemia (HoFH) (1).

Limitations of Use

- The safety and effectiveness of JUXTAPID have not been established in patients with hypercholesterolemia who do not have HoFH, including those with heterozygous familial hypercholesterolemia (HeFH) (1).
- The effect of JUXTAPID on cardiovascular morbidity and mortality has not been determined (1).

2 DOSAGE AND ADMINISTRATION

- Before treatment, measure ALT, AST, alkaline phosphatase, and total bilirubin; obtain a negative pregnancy test in females of reproductive potential; and initiate a low-fat diet supplying <20% of energy from fat (2.1).
- Initiate treatment at 5 mg once daily. Titrate dose based on acceptable safety/tolerability: increase to 10 mg daily after at least 2 weeks; and then, at a minimum of 4-week intervals, to 20 mg, 40 mg, and up to the maximum recommended dose of 60 mg daily (2.1).
- Due to reduced absorption of fat-soluble vitamins/fatty acids: Take daily vitamin E, linoleic acid, alpha-linolenic acid (ALA), eicosapentaenoic acid (EPA), and docosahexaenoic acid (DHA) supplements (2.1, 5.4).
- Take once daily, whole, with water and without food, at least 2 hours after evening meal (2.2).
- Patients with end-stage renal disease on dialysis or with baseline mild hepatic impairment should not exceed 40 mg daily (2.5, 2.6).

3 DOSAGE FORMS AND STRENGTHS

Capsules: 5 mg, 10 mg, 20 mg, and 30 mg (3).

4 CONTRAINDICATIONS

- Pregnancy (4).
- Concomitant use with strong or moderate CYP3A4 inhibitors (4).
- Moderate or severe hepatic impairment or active liver disease including unexplained persistent abnormal liver function tests (4).

5 WARNINGS AND PRECAUTIONS

- Embryo-Fetal Toxicity: May cause fetal harm. Advise females of reproductive potential of the potential risk to the fetus and to use effective contraception. Discontinue JUXTAPID if pregnancy detected (5.3, 8.1, 8.3).
- Gastrointestinal adverse reactions occur in 93% of patients and could affect absorption of concomitant oral medications (5.5).

6 ADVERSE REACTIONS

Most common adverse reactions (incidence ≥28%) are diarrhea, nausea, vomiting, dyspepsia, and abdominal pain (6.1).

To report SUSPECTED ADVERSE REACTIONS, contact Amryt Pharmaceuticals DAC at 1-855-303-2347 or FDA at 1-800-FDA-1088 or www.fda.gov/medwatch.

7 DRUG INTERACTIONS

- CYP3A4 inhibitors increase exposure to lomitapide. Strong and moderate CYP3A4 inhibitors are contraindicated with JUXTAPID. Patients must avoid grapefruit juice (4, 5.6, 7.1).
- When administered with weak CYP3A4 inhibitors, the dose of JUXTAPID should be decreased by half. The dosage of JUXTAPID may then be up-titrated to a maximum recommended dosage of 30 mg daily (2.3, 5.6, 7.2).
- Warfarin: Lomitapide increases plasma concentrations of warfarin. Monitor international normalized ratio (INR) regularly, especially with JUXTAPID dose adjustment (5.8, 7.3).
- Simvastatin and lovastatin exposure increase with JUXTAPID. Limit dose when co-administered with JUXTAPID due to myopathy risk (5.7, 7.4).
- P-glycoprotein (P-gp) Substrates: Consider dose reduction of P-gp substrate because of possible increased absorption with JUXTAPID (7.5).
- Bile Acid Sequestrants: Separate JUXTAPID dosing by at least 4 hours (7.6).

8 USE IN SPECIFIC POPULATIONS

- Lactation: Breastfeeding not recommended (8.2).
- Pediatric Patients: Safety and effectiveness not established (8.4).

FULL PRESCRIBING INFORMATION

WARNING: RISK OF HEPATOTOXICITY

JUXTAPID can cause elevations in transaminases. In the JUXTAPID clinical trial, 10 (34%) of the 29 patients treated with JUXTAPID had at least one elevation in alanine aminotransferase (ALT) or aspartate aminotransferase (AST) ≥3× upper limit of normal (ULN). There were no concomitant clinically meaningful elevations of total bilirubin, international normalized ratio (INR), or alkaline phosphatase [see Warnings and Precautions (5.1)].

JUXTAPID also increases hepatic fat, with or without concomitant increases in transaminases. The median absolute increase in hepatic fat was 6% after both 26 and 78 weeks of treatment, from 1% at baseline, measured by magnetic resonance spectroscopy. Hepatic steatosis associated with JUXTAPID treatment may be a risk factor for progressive liver disease, including steatohepatitis and cirrhosis [see Warnings and Precautions (5.1)].

Measure ALT, AST, alkaline phosphatase, and total bilirubin before initiating treatment and then ALT and AST regularly as recommended. During treatment, adjust the dose of JUXTAPID if the ALT or AST are ≥3× ULN. Discontinue JUXTAPID for clinically significant liver toxicity [see Dosage and Administration (2.4) and Warnings and Precautions (5.1)].

Because of the risk of hepatotoxicity, JUXTAPID is available only through a restricted program under a Risk Evaluation and Mitigation Strategy (REMS) called the JUXTAPID REMS Program [see Warnings and Precautions (5.2)]. Prescribe JUXTAPID only to patients with a clinical or laboratory diagnosis consistent with HoFH. The safety and effectiveness of JUXTAPID have not been established in patients with hypercholesterolemia who do not have HoFH [see Indications and Usage (1)].

1 INDICATIONS AND USAGE

1.1 Homozygous Familial Hypercholesterolemia

JUXTAPID is indicated as an adjunct to a low-fat diet and other lipid-lowering treatments, including LDL apheresis where available, to reduce low-density lipoprotein cholesterol (LDL-C), total cholesterol (TC), apolipoprotein B (apo B), and non-high-density lipoprotein cholesterol (non-HDL-C) in patients with homozygous familial hypercholesterolemia (HoFH).

Limitations of Use

- The safety and effectiveness of JUXTAPID have not been established in patients with hypercholesterolemia who do not have HoFH, including those with heterozygous familial hypercholesterolemia (HeFH).
- The effect of JUXTAPID on cardiovascular morbidity and mortality has not been determined.

2 DOSAGE AND ADMINISTRATION

2.1 Initiation and Maintenance of Therapy

Before beginning treatment with JUXTAPID:

- Measure transaminases (ALT, AST), alkaline phosphatase, and total bilirubin [see Warnings and Precautions (5.1)];
- Obtain a negative pregnancy test in females of reproductive potential prior to initiating treatment with JUXTAPID [see Contraindications (4), Warnings and Precautions (5.3), Use in Specific Populations (8.1, 8.3)];
- Initiate a low-fat diet supplying <20% of energy from fat [see Warnings and Precautions (5.5)].

The recommended starting dosage of JUXTAPID is 5 mg once daily, and the dose should be escalated gradually based on acceptable safety and tolerability. Transaminases should be measured prior to any increase in dose [see Warnings and Precautions (5.1)]. The maintenance dosage of JUXTAPID should be individualized, taking into account patient characteristics such as goal of therapy and response to treatment, to a maximum of 60 mg daily as described in Table 1. Modify dosing for patients taking concomitant weak CYP3A4 inhibitors and for those with renal impairment or baseline hepatic impairment [see Dosage and Administration (2.3), (2.5), and (2.6)]. Monitor transaminases during treatment with JUXTAPID as described in Warnings and Precautions (5.1), and reduce or withhold dosing for patients who develop transaminase values ≥3× the upper limit of normal (ULN) [see Dosage and Administration (2.4)].

Table 1: Recommended Regimen for Titrating Dosage
DOSAGE | DURATION OF ADMINISTRATION BEFORE CONSIDERING INCREASE TO NEXT DOSAGE
5 mg daily | At least 2 weeks
10 mg daily | At least 4 weeks
20 mg daily | At least 4 weeks
40 mg daily | At least 4 weeks
60 mg daily | Maximum recommended dosage

To reduce the risk of developing a fat-soluble nutrient deficiency due to JUXTAPID's mechanism of action in the small intestine, patients treated with JUXTAPID should take daily supplements that contain 400 international units vitamin E and at least 200 mg linoleic acid, 210 mg alpha-linolenic acid (ALA), 110 mg eicosapentaenoic acid (EPA), and 80 mg docosahexaenoic acid (DHA) [see Warnings and Precautions (5.4)].

2.2 Administration

JUXTAPID should be taken once daily with a glass of water, without food, at least 2 hours after the evening meal because administration with food may increase the risk of gastrointestinal adverse reactions [see Warnings and Precautions (5.5)]. Patients should swallow JUXTAPID capsules whole. Capsules should not be opened, crushed, dissolved, or chewed.

2.3 Dosing with Cytochrome P450 3A4 Inhibitors

JUXTAPID is contraindicated with concomitant use of moderate and strong cytochrome P450 3A4 (CYP3A4) inhibitors [see Contraindications (4) and Drug Interactions (7.1)].

The recommended maximum dosage of JUXTAPID is 30 mg daily with concomitant use of weak CYP3A4 inhibitors (such as alprazolam, amiodarone, amlodipine, atorvastatin, bicalutamide, cilostazol, cimetidine, cyclosporine, fluoxetine, fluvoxamine, ginkgo, goldenseal, isoniazid, lapatinib, nilotinib, pazopanib, ranitidine, ranolazine, ticagrelor, zileuton). However, the recommended maximum dosage of JUXTAPID is 40 mg daily with concomitant use of oral contraceptives.

When initiating a weak CYP3A4 inhibitor in a patient already taking JUXTAPID 10 mg daily or more, decrease the dose of JUXTAPID by half; patients taking JUXTAPID 5 mg daily may continue with the same dosage. Careful titration of JUXTAPID may then be considered according to LDL-C response and safety/tolerability to a maximum recommended dosage of 30 mg daily except when coadministered with oral contraceptives, in which case the maximum recommended lomitapide dosage is 40 mg daily [see Drug Interactions (7.2)].

2.4 Dose Modification Based on Elevated Transaminases

Table 2 summarizes recommendations for dose adjustment and monitoring for patients who develop elevated transaminases during therapy with JUXTAPID [see Warnings and Precautions (5.1)].

Table 2: Dose Adjustment and Monitoring for Patients with Elevated Transaminases
ALT OR AST | TREATMENT AND MONITORING RECOMMENDATIONS [Recommendations based on an ULN of approximately 30-40 international units/L.]
≥3× and <5× ULN | - Confirm elevation with a repeat measurement within one week. - If confirmed, reduce the dose and obtain additional liver-related tests if not already measured (such as alkaline phosphatase, total bilirubin, and INR). - Repeat tests weekly and withhold dosing if there are signs of abnormal liver function (increase in bilirubin or INR), if transaminase levels rise above 5× ULN, or if transaminase levels do not fall below 3× ULN within approximately 4 weeks. In these cases of persistent or worsening abnormalities, also investigate to identify the probable cause. - If resuming JUXTAPID after transaminases resolve to <3× ULN, consider reducing the dose and monitor liver-related tests more frequently.
≥5× ULN | - Withhold dosing, obtain additional liver-related tests if not already measured (such as alkaline phosphatase, total bilirubin, and INR), and investigate to identify the probable cause. - If resuming JUXTAPID after transaminases resolve to <3× ULN, reduce the dose and monitor liver-related tests more frequently.

If transaminase elevations are accompanied by clinical symptoms of liver injury (such as nausea, vomiting, abdominal pain, fever, jaundice, lethargy, flu-like symptoms), increases in bilirubin ≥2× ULN, or active liver disease, discontinue treatment with JUXTAPID and investigate to identify the probable cause [see Warnings and Precautions (5.1)].

2.5 Dosing in Patients with Renal Impairment

Patients with end-stage renal disease receiving dialysis should not exceed 40 mg daily. There are no data available to guide dosing in other patients with renal impairment [see Use in Specific Populations (8.6)].

2.6 Dosing in Patients with Baseline Hepatic Impairment

Patients with mild hepatic impairment (Child-Pugh A) should not exceed 40 mg daily [see Use in Specific Populations (8.7)].

3 DOSAGE FORMS AND STRENGTHS

5 mg: Orange/orange hard gelatin capsule printed with black ink "A733" and "5 mg"

10 mg: Orange/white hard gelatin capsule printed with black ink "A733" and "10 mg"

20 mg: White/white hard gelatin capsule printed with black ink "A733" and "20 mg"

30 mg: Orange/yellow hard gelatin capsule printed with black ink "A733" and "30 mg"

4 CONTRAINDICATIONS

JUXTAPID is contraindicated in the following conditions:

- Pregnancy [see Warnings and Precautions (5.3) and Use in Specific Populations (8.1)].
- Concomitant administration of JUXTAPID with moderate or strong CYP3A4 inhibitors, as this can increase JUXTAPID exposure [see Warnings and Precautions (5.6), Drug Interactions (7.1), and Clinical Pharmacology (12.3)].
- Patients with moderate or severe hepatic impairment (based on Child-Pugh category B or C) and patients with active liver disease, including unexplained persistent elevations of serum transaminases [see Warnings and Precautions (5.1) and Use in Specific Populations (8.7)].

5 WARNINGS AND PRECAUTIONS

5.1 Risk of Hepatotoxicity

JUXTAPID can cause elevations in transaminases and hepatic steatosis, as described below [see Warnings and Precautions (5.2)]. To what extent JUXTAPID-associated hepatic steatosis promotes the elevations in transaminases is unknown. Although cases of hepatic dysfunction (elevated transaminases with increase in bilirubin or INR) or hepatic failure have not been reported, there is concern that JUXTAPID could induce steatohepatitis, which can progress to cirrhosis over several years. The clinical studies supporting the safety and efficacy of JUXTAPID in HoFH would have been unlikely to detect this adverse outcome given their size and duration [see Clinical Studies (14)].

Elevation of Transaminases

Elevations in transaminases (alanine aminotransferase [ALT] and/or aspartate aminotransferase [AST]) are associated with JUXTAPID. In the clinical trial, 10 (34%) of the 29 patients with HoFH had at least one elevation in ALT or AST ≥3× ULN, and 4 (14%) of the patients had at least one elevation in ALT or AST ≥5× ULN. There were no concomitant or subsequent clinically meaningful elevations in bilirubin, INR, or alkaline phosphatase [see Adverse Reactions (6.1)].

During the 78-week HoFH clinical trial, no patients discontinued prematurely because of elevated transaminases. Among the 19 patients who subsequently enrolled in the HoFH extension study, one discontinued because of increased transaminases that persisted despite several dose reductions, and one temporarily discontinued because of markedly elevated transaminases (ALT 24× ULN, AST 13× ULN) that had several possible causes, including a drug-drug interaction between JUXTAPID and the strong CYP3A4 inhibitor clarithromycin [see Drug Interactions (7.1)].

Monitoring of Transaminases

Before initiating JUXTAPID and during treatment, monitor transaminases as recommended in Table 3.

Table 3: Recommendations for Monitoring Transaminases
TIME | RECOMMENDATIONS
Before initiating treatment | - Measure ALT, AST, alkaline phosphatase, and total bilirubin. - If abnormal, consider initiating JUXTAPID only after an appropriate work-up and the baseline abnormalities have been explained or resolved. - JUXTAPID is contraindicated in patients with moderate or severe hepatic impairment, or active liver disease, including unexplained persistent elevations of serum transaminases [see Contraindications (4)].
During the first year | - Measure liver-related tests (ALT and AST, at a minimum) prior to each increase in dose or monthly, whichever occurs first.
After the first year | - Measure liver-related tests (ALT and AST, at a minimum) at least every 3 months and before any increase in dose.
At any time during treatment | - If transaminases are abnormal, reduce or withhold dosing of JUXTAPID and monitor as recommended [see Dosage and Administration (2.4)]. - Discontinue JUXTAPID for persistent or clinically significant elevations. - If transaminase elevations are accompanied by clinical symptoms of liver injury (such as nausea, vomiting, abdominal pain, fever, jaundice, lethargy, flu-like symptoms), increases in bilirubin ≥2× ULN, or active liver disease, discontinue treatment with JUXTAPID and identify the probable cause.

Hepatic Steatosis

JUXTAPID increases hepatic fat, with or without concomitant increases in transaminases. Hepatic steatosis is a risk factor for progressive liver disease, including steatohepatitis and cirrhosis. The long-term consequences of hepatic steatosis associated with JUXTAPID treatment are unknown. During the HoFH clinical trial, the median absolute increase in hepatic fat was 6% after both 26 weeks and 78 weeks of treatment, from 1% at baseline, measured by magnetic resonance spectroscopy (MRS) [see Adverse Reactions (6.1)]. Clinical data suggest that hepatic fat accumulation is reversible after stopping treatment with JUXTAPID, but whether histological sequelae remain is unknown, especially after long-term use; protocol liver biopsies were not performed in the HoFH clinical trial.

Alcohol may increase levels of hepatic fat and induce or exacerbate liver injury. It is recommended that patients taking JUXTAPID should not consume more than one alcoholic drink per day.

Caution should be exercised when JUXTAPID is used with other medications known to have potential for hepatotoxicity, such as isotretinoin, amiodarone, acetaminophen (>4 g/day for ≥3 days/week), methotrexate, tetracyclines, and tamoxifen. The effect of concomitant administration of JUXTAPID with other hepatotoxic medications is unknown. More frequent monitoring of liver-related tests may be warranted.

JUXTAPID has not been studied concomitantly with other LDL-lowering agents that can also increase hepatic fat. Therefore, the combined use of such agents is not recommended.

5.2 JUXTAPID REMS Program

Because of the risk of hepatotoxicity associated with JUXTAPID therapy, JUXTAPID is available through a restricted program under the REMS. Under the JUXTAPID REMS, only certified healthcare providers and pharmacies may prescribe and distribute JUXTAPID. Further information is available at www.JUXTAPIDREMSProgram.com or by telephone at 1-85-JUXTAPID (1-855-898-2743).

5.3 Embryo-Fetal Toxicity

Based on findings from animal studies, JUXTAPID use is contraindicated in pregnancy since it may cause fetal harm [see Contraindications (4), Use in Specific Populations (8.1, 8.3)]. In animal reproduction studies in rats and ferrets, embryonic death and fetal malformations were observed at clinically relevant exposures. Females of reproductive potential should have a negative pregnancy test before starting JUXTAPID. Advise females of reproductive potential to use effective contraception during therapy with JUXTAPID and for two weeks after the final dose. If pregnancy is detected, discontinue JUXTAPID.

5.4 Reduced Absorption of Fat-Soluble Vitamins and Serum Fatty Acids

Given its mechanism of action in the small intestine, JUXTAPID may reduce the absorption of fat-soluble nutrients. In the HoFH clinical trial, patients were provided daily dietary supplements of vitamin E, linoleic acid, alpha-linolenic acid (ALA), eicosapentaenoic acid (EPA), and docosahexaenoic acid (DHA). In this trial, the median levels of serum vitamin E, ALA, linoleic acid, EPA, DHA, and arachidonic acid decreased from baseline to Week 26 but remained above the lower limit of the reference range. Adverse clinical consequences of these reductions were not observed with JUXTAPID treatment of up to 78 weeks. Patients treated with JUXTAPID should take daily supplements that contain 400 international units vitamin E and at least 200 mg linoleic acid, 210 mg ALA, 110 mg EPA, and 80 mg DHA [see Dosage and Administration (2.1)]. Patients with chronic bowel or pancreatic diseases that predispose to malabsorption may be at increased risk for deficiencies in these nutrients with use of JUXTAPID.

5.5 Gastrointestinal Adverse Reactions

Gastrointestinal adverse reactions were reported by 27 (93%) of 29 patients in the HoFH clinical trial. Diarrhea occurred in 79% of patients, nausea in 65%, dyspepsia in 38%, and vomiting in 34%. Other reactions reported by at least 20% of patients include abdominal pain, abdominal discomfort, abdominal distension, constipation, and flatulence [see Adverse Reactions (6)].

Gastrointestinal adverse reactions of severe intensity were reported by 6 (21%) of 29 patients in the HoFH clinical trial, with the most common being diarrhea (4 patients, 14%); vomiting (3 patients, 10%); and abdominal pain, distension, and/or discomfort (2 patients, 7%). Gastrointestinal reactions contributed to the reasons for early discontinuation from the trial for 4 (14%) patients.

There have been postmarketing reports of severe diarrhea with the use of JUXTAPID, including patients being hospitalized because of diarrhea-related complications such as volume depletion. Monitor patients who are more susceptible to complications from diarrhea, such as older patients and patients taking drugs that can lead to volume depletion or hypotension. Instruct patients to stop JUXTAPID and contact their healthcare provider if severe diarrhea occurs or if they experience symptoms of volume depletion such as lightheadedness, decreased urine output, or tiredness. In such cases, consider reducing the dose or suspending use of JUXTAPID.

Absorption of concomitant oral medications may be affected in patients who develop diarrhea or vomiting.

To reduce the risk of gastrointestinal adverse events, patients should adhere to a low-fat diet supplying <20% of energy from fat and the dosage of JUXTAPID should be increased gradually [see Dosage and Administration (2.1) and (2.2)].

5.6 Concomitant Use of CYP3A4 Inhibitors

CYP3A4 inhibitors increase the exposure of lomitapide, with strong inhibitors increasing exposure approximately 27-fold. Concomitant use of moderate or strong CYP3A4 inhibitors with JUXTAPID is contraindicated [see Drug Interactions (7.1)]. In the JUXTAPID clinical trials, one patient with HoFH developed markedly elevated transaminases (ALT 24× ULN, AST 13× ULN) within days of initiating the strong CYP3A4 inhibitor clarithromycin. If treatment with moderate or strong CYP3A4 inhibitors is unavoidable, JUXTAPID should be stopped during the course of treatment.

Grapefruit juice must be omitted from the diet while being treated with JUXTAPID.

Weak CYP3A4 inhibitors can increase the exposure of lomitapide approximately 2-fold; therefore, when JUXTAPID is administered with weak CYP3A4 inhibitors, the dose of JUXTAPID should be decreased by half. Careful titration may then be considered based on LDL-C response and safety/tolerability to a maximum recommended dosage of 30 mg daily except when coadministered with oral contraceptives, in which case the maximum recommended lomitapide dosage is 40 mg daily [see Dosage and Administration (2.3) and Drug Interactions (7.2)].

5.7 Risk of Myopathy with Concomitant Use of Simvastatin or Lovastatin

The risk of myopathy, including rhabdomyolysis, with simvastatin and lovastatin monotherapy is dose related. Lomitapide approximately doubles the exposure to simvastatin; therefore, it is recommended to reduce the dose of simvastatin by 50% when initiating JUXTAPID [see Clinical Pharmacology (12.3)]. While taking JUXTAPID, limit simvastatin dosage to 20 mg daily (or 40 mg daily for patients who have previously tolerated simvastatin 80 mg daily for at least one year without evidence of muscle toxicity). Refer to the simvastatin prescribing information for additional dosing recommendations.

Interaction between lovastatin and lomitapide has not been studied. However, the metabolizing enzymes and transporters responsible for the disposition of lovastatin and simvastatin are similar, suggesting that JUXTAPID may increase the exposure of lovastatin; therefore, reducing the dose of lovastatin should be considered when initiating JUXTAPID.

5.8 Risk of Supratherapeutic or Subtherapeutic Anticoagulation with Warfarin

JUXTAPID increases the plasma concentrations of warfarin. Increases in the dose of JUXTAPID may lead to supratherapeutic anticoagulation, and decreases in the dose of JUXTAPID may lead to subtherapeutic anticoagulation. Difficulty controlling INR contributed to early discontinuation from the HoFH clinical trial for one of five patients taking concomitant warfarin. Patients taking warfarin should undergo regular monitoring of the INR, especially after any changes in JUXTAPID dosage. The dose of warfarin should be adjusted as clinically indicated [see Drug Interactions (7.3)].

5.9 Risk of Malabsorption with Rare Hereditary Disorders of Galactose Intolerance

Patients with rare, hereditary problems of galactose intolerance, the Lapp lactase deficiency, or glucose-galactose malabsorption should avoid JUXTAPID as this may result in diarrhea and malabsorption.

6 ADVERSE REACTIONS

The following important adverse reactions have been observed and are discussed in detail in other sections of the label:

- Risk of hepatotoxicity [see Warnings and Precautions (5.1)]
- Reduced absorption of fat-soluble vitamins, and serum fatty acids [see Warnings and Precautions (5.4)]
- Gastrointestinal adverse reactions [see Warnings and Precautions (5.5)]

6.1 Clinical Trials Experience

Because clinical trials are conducted under widely varying conditions, adverse reaction rates observed in the clinical trials of a drug cannot be directly compared to rates in the clinical trials of another drug and may not reflect the rates observed in practice.

One single-arm, open-label, 78-week trial has been conducted in 29 patients with HoFH, 23 of whom completed at least one year of treatment. The initial dosage of JUXTAPID was 5 mg daily, with titration up to 60 mg daily during an 18-week period based on safety and tolerability. In this trial, the mean age was 30.7 years (range, 18 to 55 years), 16 (55%) patients were men, 25 (86%) patients were Caucasian, 2 (7%) were Asian, 1 (3%) was African American, and 1 (3%) was multi-racial [see Clinical Studies (14)].

Five (17%) of the 29 patients with HoFH that participated in the clinical trial discontinued treatment due to an adverse reaction. The adverse reactions that contributed to treatment discontinuations included diarrhea (2 patients; 7%) and abdominal pain, nausea, gastroenteritis, weight loss, headache, and difficulty controlling INR on warfarin (1 patient each; 3%).

The most common adverse reactions were gastrointestinal, reported by 27 (93%) of 29 patients. Adverse reactions reported by ≥8 (28%) patients in the HoFH clinical trial included diarrhea, nausea, vomiting, dyspepsia, and abdominal pain. Other common adverse reactions, reported by 5 to 7 (17-24%) patients, included weight loss, abdominal discomfort, abdominal distension, constipation, flatulence, increased ALT, chest pain, influenza, nasopharyngitis, and fatigue.

The adverse reactions reported in at least 10% of patients during the HoFH clinical trial are presented in Table 4.

Table 4: Adverse Reactions Reported in ≥10% of Patients in the Clinical Trial in HoFH
ADVERSE REACTION | N (%)
Gastrointestinal Disorders
Diarrhea | 23 (79)
Nausea | 19 (65)
Dyspepsia | 11 (38)
Vomiting | 10 (34)
Abdominal pain | 10 (34)
Abdominal discomfort | 6 (21)
Abdominal distension | 6 (21)
Constipation | 6 (21)
Flatulence | 6 (21)
Gastroesophageal reflux disease | 3 (10)
Defecation urgency | 3 (10)
Rectal tenesmus | 3 (10)
Infections
Influenza | 6 (21)
Nasopharyngitis | 5 (17)
Gastroenteritis | 4 (14)
Investigations
Decreased weight | 7 (24)
Increased ALT | 5 (17)
General Disorders
Chest pain | 7 (24)
Fatigue | 5 (17)
Fever | 3 (10)
Musculoskeletal Disorders
Back pain | 4 (14)
Nervous System Disorders
Headache | 3 (10)
Dizziness | 3 (10)
Respiratory Disorders
Pharyngolaryngeal pain | 4 (14)
Nasal congestion | 3 (10)
Cardiac Disorders
Angina pectoris | 3 (10)
Palpitations | 3 (10)

Adverse reactions of severe intensity were reported by 8 (28%) of 29 patients, with the most common being diarrhea (4 patients, 14%), vomiting (3 patients, 10%), increased ALT or hepatotoxicity (3 patients, 10%), and abdominal pain, distension, and/or discomfort (2 patients, 7%).

Transaminase Elevations

During the HoFH clinical trial, 10 (34%) of 29 patients had at least one elevation in ALT and/or AST ≥3× ULN (see Table 5). No clinically meaningful elevations in total bilirubin or alkaline phosphatase were observed. Transaminases typically fell within one to four weeks of reducing the dose or withholding JUXTAPID.

Table 5: Patient Incidence of Transaminase Elevations During the HoFH Clinical Trial
 | N (%)
Total Patients | 29
Maximum ALT
≥3 to <5 × ULN | 6 (21%)
≥5 to <10 × ULN | 3 (10%)
≥10 to <20 × ULN | 1 (3%)
≥20 × ULN | 0
Maximum AST
≥3 to <5 × ULN | 5 (17%)
≥5 to <10 × ULN | 1 (3%)
≥10 to <20 × ULN | 0
≥20 × ULN | 0
Upper limits of normal (ULN) ranged from 33-41 international units/L for ALT and 36-43 international units/L for AST.

Among the 19 patients who enrolled in an extension study following the HoFH clinical trial, one discontinued because of increased transaminases that persisted despite several dose reductions, and one temporarily discontinued because of markedly elevated transaminases (ALT 24× ULN, AST 13× ULN) that had several possible causes, including a drug-drug interaction between JUXTAPID and the strong CYP3A4 inhibitor clarithromycin [see Drug Interactions (7.1)].

Hepatic Steatosis

Hepatic fat was prospectively measured using magnetic resonance spectroscopy (MRS) in all eligible patients during the HoFH clinical trial. After 26 weeks, the median absolute increase in hepatic fat from baseline was 6%, and the mean absolute increase was 8% (range, 0% to 30%). After 78 weeks, the median absolute increase in hepatic fat from baseline was 6%, and the mean absolute increase was 7% (range, 0% to 18%). Among the 23 patients with evaluable data, on at least one occasion during the trial, 18 (78%) exhibited an increase in hepatic fat >5% and 3 (13%) exhibited an increase >20%. Data from individuals who had repeat measurements after stopping JUXTAPID show that hepatic fat accumulation is reversible, but whether histological sequelae remain is unknown.

6.2 Postmarketing Experience

The following adverse reactions have been identified during post-approval use of JUXTAPID. Because these reactions are reported voluntarily from a population of uncertain size, it is not possible to reliably estimate their frequency or establish a causal relationship to JUXTAPID exposure.

Musculoskeletal disorders: Myalgia

Skin reactions: Alopecia

7 DRUG INTERACTIONS

7.1 Moderate and Strong CYP3A4 Inhibitors

A strong CYP3A4 inhibitor has been shown to increase lomitapide exposure approximately 27-fold [see Clinical Pharmacology (12.3)]. Concomitant use of strong CYP3A4 inhibitors (such as boceprevir, clarithromycin, conivaptan, indinavir, itraconazole, ketoconazole, lopinavir/ritonavir, nefazodone, nelfinavir, posaconazole, ritonavir, saquinavir, telaprevir, telithromycin, tipranavir/ritonavir, voriconazole) with lomitapide is contraindicated. Concomitant use of moderate CYP3A4 inhibitors (such as amprenavir, aprepitant, atazanavir, ciprofloxacin, crizotinib, darunavir/ritonavir, diltiazem, erythromycin, fluconazole, fosamprenavir, imatinib, verapamil) has not been studied, but concomitant use with lomitapide is contraindicated since lomitapide exposure will likely increase significantly in the presence of these inhibitors.

Patients must avoid grapefruit juice while taking JUXTAPID [see Contraindications (4), Warnings and Precautions (5.6), and Clinical Pharmacology (12.3)].

7.2 Weak CYP3A4 Inhibitors

Weak CYP3A4 inhibitors (such as alprazolam, amiodarone, amlodipine, atorvastatin, bicalutamide, cilostazol, cimetidine, cyclosporine, fluoxetine, fluvoxamine, ginkgo, goldenseal, isoniazid, lapatinib, nilotinib, pazopanib, ranitidine, ranolazine, ticagrelor, zileuton) can increase lomitapide exposure approximately 2-fold [see Clinical Pharmacology (12.3)]. When administered with weak CYP3A4 inhibitors, the dose of JUXTAPID should be decreased by half. Careful titration of JUXTAPID may then be considered based on LDL-C response and safety/tolerability to a maximum recommended dosage of 30 mg daily except when coadministered with oral contraceptives, in which case the maximum recommended lomitapide dosage is 40 mg daily [see Dosage and Administration (2.3), Warnings and Precautions (5.6), and Clinical Pharmacology (12.3)].

7.3 Warfarin

Lomitapide increases plasma concentrations of both R(+)-warfarin and S(-)-warfarin by approximately 30% and increased the INR 22%. Patients taking warfarin should undergo regular monitoring of INR, particularly after any changes in lomitapide dosage. The dose of warfarin should be adjusted as clinically indicated [see Warnings and Precautions (5.8)].

7.4 Simvastatin and Lovastatin

The risk of myopathy, including rhabdomyolysis, with simvastatin and lovastatin monotherapy is dose related. Lomitapide approximately doubles the exposure of simvastatin; therefore, the recommended dose of simvastatin should be reduced by 50% when initiating JUXTAPID [see Clinical Pharmacology (12.3)]. While taking JUXTAPID, limit simvastatin dosage to 20 mg daily (or 40 mg daily for patients who have previously tolerated simvastatin 80 mg daily for at least one year without evidence of muscle toxicity). Refer to the simvastatin prescribing information for simvastatin dosing recommendations.

Interaction between lovastatin and lomitapide has not been studied. However, the metabolizing enzymes and transporters responsible for the disposition of lovastatin and simvastatin are similar, suggesting that JUXTAPID may increase the exposure of lovastatin; therefore, reducing the dose of lovastatin should be considered when initiating JUXTAPID.

7.5 P-glycoprotein Substrates

Lomitapide is an inhibitor of P-glycoprotein (P-gp). Coadministration of lomitapide with P-gp substrates (such as aliskiren, ambrisentan, colchicine, dabigatran etexilate, digoxin, everolimus, fexofenadine, imatinib, lapatinib, maraviroc, nilotinib, posaconazole, ranolazine, saxagliptin, sirolimus, sitagliptin, talinolol, tolvaptan, topotecan) may increase the absorption of P-gp substrates. Dose reduction of the P-gp substrate should be considered when used concomitantly with lomitapide.

7.6 Bile Acid Sequestrants

JUXTAPID has not been tested for interaction with bile acid sequestrants. Administration of JUXTAPID and bile acid sequestrants should be separated by at least 4 hours since bile acid sequestrants can interfere with the absorption of oral medications.

8 USE IN SPECIFIC POPULATIONS

8.1 Pregnancy

Pregnancy Exposure Registry

There is a pregnancy exposure registry that monitors pregnancy outcomes in women exposed to JUXTAPID during pregnancy. For additional information visit www.JUXTAPID.com or call the Global Lomitapide Pregnancy Exposure Registry (PER) at 1-877-902-4099. Healthcare professionals are encouraged to call the PER at 1-877-902-4099 to enroll patients who become pregnant during JUXTAPID treatment.

Risk Summary

Based on findings from animal studies, JUXTAPID use is contraindicated in pregnancy since it may cause fetal harm [see Contraindications (4), Warnings and Precautions (5.3)]. Available human data are insufficient to draw conclusions about any drug-associated risks for major birth defects, miscarriage, or adverse maternal or fetal outcomes. However, in animal reproduction studies, lomitapide was teratogenic in rats at clinically relevant exposures and in ferrets at exposures estimated to be less than human therapeutic exposure at 60 mg when administered during organogenesis, based on AUC comparisons. Embryo-fetal lethality was observed in rabbits at 6-times the maximum recommended human dose (MRHD) of 60 mg based on body surface area. If pregnancy is detected, discontinue JUXTAPID.

The estimated background risk of major birth defects and miscarriage for the indicated population is unknown. In the U.S. general population, the estimated background risks of major birth defects and miscarriage in clinically recognized pregnancies is 2-4% and 15-20%, respectively.

Data

Animal Data

Oral gavage doses of 0.04, 0.4, or 4 mg/kg/day lomitapide given to pregnant rats from gestation day 6 through organogenesis were associated with fetal malformations at ≥2-times human exposure at the MRHD (60 mg) based on plasma AUC comparisons. Fetal malformations included umbilical hernia, gastroschisis, imperforate anus, alterations in heart shape and size, limb malrotations, skeletal malformations of the tail, and delayed ossification of cranial, vertebral and pelvic bones.

Oral gavage doses of 1.6, 4, 10, or 25 mg/kg/day lomitapide given to pregnant ferrets from gestation day 12 through organogenesis were associated with both maternal toxicity and fetal malformations at exposures that ranged from less than the human exposure at the MRHD to 5-times the human exposure at the MRHD. Fetal malformations included umbilical hernia, medially rotated or short limbs, absent or fused digits on paws, cleft palate, open eye lids, low-set ears, and kinked tail.

Oral gavage doses of 0.1, 1, or 10 mg/kg/day lomitapide given to pregnant rabbits from gestation day 6 through organogenesis were not associated with adverse effects at systemic exposures up to 3-times the MRHD of 60 mg based on body surface area comparison. Treatment at doses of ≥20 mg/kg/day, ≥6-times the MRHD, resulted in embryo-fetal lethality.

Pregnant female rats given oral gavage doses of 0.1, 0.3, or 1 mg/kg/day lomitapide from gestation day 7 through termination of nursing on lactation day 20 were associated with malformations at systemic exposures equivalent to human exposure at the MRHD of 60 mg based on AUC. Increased pup mortality occurred at 4-times the MRHD.

8.2 Lactation

Risk Summary

There are no data on the presence of lomitapide in human or animal milk, effects on the breastfed infant or on milk production. Because of the potential for serious adverse reactions, including hepatotoxicity, advise patients that breastfeeding is not recommended during treatment with JUXTAPID.

8.3 Females and Males of Reproductive Potential

Pregnancy Testing

Females of reproductive potential should have a negative pregnancy test before starting JUXTAPID.

Contraception

Based on animal studies, JUXTAPID may cause fetal harm when administered to pregnant women [see Use in Specific Populations (8.1)]. Advise females of reproductive potential to use effective contraception during treatment with JUXTAPID and for two weeks after the final dose.

The use of JUXTAPID may result in reduced efficacy of oral contraceptives if vomiting or diarrhea occurs. Advise patients using oral contraceptives and who experience vomiting or diarrhea to use an effective alternative contraceptive method until 7 days after resolution of symptoms [see Drug Interactions (7.2)].

8.4 Pediatric Use

Safety and effectiveness have not been established in pediatric patients.

8.5 Geriatric Use

Clinical studies of JUXTAPID did not include sufficient numbers of patients aged 65 years and over to determine whether they respond differently from younger patients. Other reported clinical experience has not identified differences in responses between the elderly and younger patients. In general, dosing for an elderly patient should be cautious, reflecting the greater frequency of decreased hepatic, renal, or cardiac function, and of concomitant disease or other drug therapy.

8.6 Renal Impairment

Patients with end-stage renal disease receiving dialysis should not exceed 40 mg daily since lomitapide exposure in these patients increased approximately 50% compared with healthy volunteers. Effects of mild, moderate, and severe renal impairment, including those with end-stage renal disease not yet receiving dialysis, on lomitapide exposure have not been studied. However, it is possible that patients with renal impairment who are not yet receiving dialysis may experience increases in lomitapide exposure exceeding 50% [see Clinical Pharmacology (12.3)].

8.7 Hepatic Impairment

Patients with mild hepatic impairment (Child-Pugh A) should not exceed 40 mg daily since the lomitapide exposure in these patients increased approximately 50% compared with healthy volunteers. JUXTAPID is contraindicated in patients with moderate (Child-Pugh B) or severe (Child-Pugh C) hepatic impairment since the lomitapide exposure in patients with moderate hepatic impairment increased 164% compared with healthy volunteers [see Contraindications (4) and Clinical Pharmacology (12.3)].

10 OVERDOSAGE

There is no specific treatment in the event of overdose of JUXTAPID. In the event of overdose, the patient should be treated symptomatically and supportive measures instituted as required. Liver-related tests should be monitored. Hemodialysis is unlikely to be beneficial given that lomitapide is highly protein bound.

11 DESCRIPTION

JUXTAPID capsules contain lomitapide mesylate, a synthetic lipid-lowering agent for oral administration.

The chemical name of lomitapide mesylate is N-(2,2,2-trifluoroethyl)-9-[4-[4-[[[4'-(trifluoromethyl)[1,1'-biphenyl]-2-yl]carbonyl]amino]-1-piperidinyl]butyl]-9H-fluorene-9-carboxamide, methanesulfonate salt. Its structural formula is:

The empirical formula for lomitapide mesylate is C39H37F6N3O2 ∙ CH4O3S and its molecular weight is 789.8.

Lomitapide mesylate is a white to off-white powder that is slightly soluble in aqueous solutions of pH 2 to 5. Lomitapide mesylate is freely soluble in acetone, ethanol, and methanol; soluble in 2-butanol, methylene chloride, and acetonitrile; sparingly soluble in 1-octanol and 2-propanol; slightly soluble in ethyl acetate; and insoluble in heptane.

Each JUXTAPID capsule contains lomitapide mesylate equivalent to 5, 10, 20, or 30 mg lomitapide free base and the following inactive ingredients: pregelatinized starch, sodium starch glycolate, microcrystalline cellulose, lactose monohydrate, silicon dioxide and magnesium stearate. The capsule shells of all strengths contain gelatin and titanium dioxide; the 5 mg, 10 mg and 30 mg capsules also contain red iron oxide; and the 30 mg capsules also contain yellow iron oxide. The imprinting ink contains shellac, black iron oxide, and propylene glycol.

12 CLINICAL PHARMACOLOGY

12.1 Mechanism of Action

JUXTAPID directly binds and inhibits microsomal triglyceride transfer protein (MTP), which resides in the lumen of the endoplasmic reticulum, thereby preventing the assembly of apo B-containing lipoproteins in enterocytes and hepatocytes. This inhibits the synthesis of chylomicrons and VLDL. The inhibition of the synthesis of VLDL leads to reduced levels of plasma LDL-C.

12.2 Pharmacodynamics

Effects on QT Interval

At a concentration 23 times the Cmax of the maximum recommended dose, lomitapide does not prolong QTc to any clinically relevant extent.

12.3 Pharmacokinetics

Absorption

Upon oral administration of a single 60-mg dose of JUXTAPID, the lomitapide tmax is around 6 hours in healthy volunteers. The absolute bioavailability of lomitapide is approximately 7%. Lomitapide pharmacokinetics is approximately dose-proportional for oral single doses from 10-100 mg.

Distribution

The mean lomitapide volume of distribution at steady state is 985-1292 liters. Lomitapide is 99.8% plasma-protein bound.

Metabolism

Lomitapide is metabolized extensively by the liver. The metabolic pathways include oxidation, oxidative N-dealkylation, glucuronide conjugation, and piperidine ring opening. Cytochrome P450 (CYP) 3A4 metabolizes lomitapide to its major metabolites, M1 and M3, as detected in plasma. The oxidative N-dealkylation pathway breaks the lomitapide molecule into M1 and M3. M1 is the moiety that retains the piperidine ring, whereas M3 retains the rest of the lomitapide molecule in vitro. CYPs 1A2, 2B6, 2C8, and 2C19 may metabolize lomitapide to a small extent to M1. M1 and M3 do not inhibit activity of microsomal triglyceride transfer protein in vitro.

Excretion

In a mass-balance study, a mean of 59.5% and 33.4% of the dose was excreted in the urine and feces, respectively. In another mass-balance study, a mean of 52.9% and 35.1% of the dose was excreted in the urine and feces, respectively. Lomitapide was not detectable in urine samples. M1 is the major urinary metabolite. Lomitapide is the major component in the feces. The mean lomitapide terminal half-life is 39.7 hours.

Specific Populations

Hepatic Impairment

A single-dose, open-label study was conducted to evaluate the pharmacokinetics of 60 mg lomitapide in healthy volunteers with normal hepatic function compared with patients with mild (Child-Pugh A) and moderate (Child-Pugh B) hepatic impairment. In patients with moderate hepatic impairment, lomitapide AUC and Cmax were 164% and 361% higher, respectively, compared with healthy volunteers. In patients with mild hepatic impairment, lomitapide AUC and Cmax were 47% and 4% higher, respectively, compared with healthy volunteers. Lomitapide has not been studied in patients with severe hepatic impairment (Child-Pugh score 10-15) [see Dosage and Administration (2.6), Contraindications (4), Warnings and Precautions (5.1), and Use in Specific Populations (8.7)].

Renal Impairment

A single-dose, open-label study was conducted to evaluate the pharmacokinetics of 60 mg lomitapide in patients with end-stage renal disease receiving hemodialysis compared with healthy volunteers with normal renal function. Healthy volunteers had estimated creatinine clearance >80 mL/min by the Cockcroft-Gault equation. Compared with healthy volunteers, lomitapide AUC0-inf and Cmax were 40% and 50% higher, respectively, in patients with end-stage renal disease receiving hemodialysis. Effects of mild, moderate, and severe renal impairment as well as end-stage renal disease not yet on dialysis on lomitapide exposure have not been studied [see Dosage and Administration (2.5) and Use in Specific Populations (8.6)].

Drug Interactions

[see Dosage and Administration (2.3), Contraindications (4), Warnings and Precautions (5.6), (5.7), (5.8), and Drug Interactions (7)].

In vitro Assessment of Drug Interactions

Lomitapide does not induce CYPs 1A2, 3A4, or 2B6. Lomitapide inhibits CYP3A4. Lomitapide does not inhibit CYPs 1A2, 2B6, 2C9, 2C19, 2D6, or 2E1. M1 and M3 do not induce CYPs 1A2, 3A4, or 2B6. M1 and M3 do not inhibit CYPs 1A2, 2A6, 2B6, 2C8, 2C9, 2C19, 2D6, 2E1, or 3A4. Lomitapide is not a P-gp substrate. Lomitapide inhibits P-gp but does not inhibit breast cancer resistance protein (BCRP).

Effects of other Drugs on Lomitapide

Table 6 summarizes the effect of coadministered drugs on lomitapide AUC and Cmax.

Table 6: Effect of Coadministered Drugs on Lomitapide Systemic Exposure
COADMINISTERED DRUG | DOSING OF COADMINISTERED DRUG | DOSING OF LOMITAPIDE | RATIO OF LOMITAPIDE EXPOSURE WITH/WITHOUT COADMINISTERED DRUG NO EFFECT = 1
COADMINISTERED DRUG | DOSING OF COADMINISTERED DRUG |  | AUC | Cmax
Contraindicated with lomitapide [see Contraindications (4) and Warnings and Precautions (5.6)]
Ketoconazole | 200 mg BID for 9 days | 60 mg single dose | ↑ 27 | ↑ 15
Adjustment necessary when coadministered with lomitapide [see Dosage and Administration (2.3) and Warnings and Precautions (5.6)]
 |  |  | AUC | Cmax
Atorvastatin | 80 mg QD | 20 mg single dose | ↑2 | ↑2.1
Ethinyl Estradiol (EE) / norgestimate | 0.035 mg EE/ 0.25 mg norgestimate QD | 20 mg single dose | ↑1.3 | ↑1.4
BID = twice daily; QD = once daily
↑ = increase

Effect of Lomitapide on other Drugs

Table 7 summarizes the effects of lomitapide on the AUC and Cmax of coadministered drugs.

Table 7: Effect of Lomitapide on the Systemic Exposure of Coadministered Drugs
COADMINISTERED DRUG | DOSING OF COADMINISTERED DRUG | DOSING OF LOMITAPIDE | CHANGE OF COADMINISTERED DRUG EXPOSURE WITH / WITHOUT LOMITAPIDE
COADMINISTERED DRUG | DOSING OF COADMINISTERED DRUG | DOSING OF LOMITAPIDE |  | AUC | Cmax
Dosage adjustment necessary when coadministered with lomitapide
Simvastatin [Limit simvastatin dosage to 20 mg daily (or 40 mg daily for patients who have previously tolerated simvastatin 80 mg daily for at least one year without evidence of muscle toxicity). Refer to the simvastatin prescribing information for additional dosing recommendations.] | 40 mg single dose | 60 mg QD × 7 days | Simvastatin | ↑ 99% | ↑ 102%
 |  |  | Simvastatin acid | ↑ 71% | ↑ 57%
 | 20 mg single dose | 10 mg QD × 7 days | Simvastatin | ↑ 62% | ↑65%
 |  |  | Simvastatin acid | ↑ 39% | ↑ 35%
Warfarin [Patients taking warfarin should undergo regular monitoring of the INR, especially after any changes in lomitapide dosage.] | 10 mg single dose | 60 mg QD × 12 days | R(+) warfarin | ↑ 28% | ↑ 14%
 |  |  | S(-) warfarin | ↑ 30% | ↑ 15%
 |  |  | INR | ↑ 7% | ↑ 22%
No dosing adjustments required for the following:
Atorvastatin | 20 mg single dose | 60 mg QD × 7 days | Atorvastatin acid | ↑ 52% | ↑63%
 | 20 mg single dose | 10 mg QD × 7 days | Atorvastatin acid | ↑ 11% | ↑19%
Rosuvastatin | 20 mg single dose | 60 mg QD × 7 days | Rosuvastatin | ↑ 32% | ↑ 4%
 | 20 mg single dose | 10 mg QD × 7 days | Rosuvastatin | ↑ 2% | ↑ 6%
Fenofibrate, micronized | 145 mg single dose | 10 mg QD × 7 days | Fenofibric acid | ↓ 10% | ↓29%
Ezetimibe | 10 mg single dose | 10 mg QD × 7 days | Total ezetimibe | ↑ 6% | ↑ 3%
Extended release niacin | 1000 mg single dose | 10 mg QD × 7 days | Nicotinic acid | ↑ 10% | ↑ 11%
 |  |  | Nicotinuric acid | ↓ 21% | ↓ 15%
Ethinyl estradiol | 0.035 mg QD × 28 days | 50 mg QD × 8 days | Ethinyl estradiol | ↓ 8% | ↓ 8%
Norgestimate | 0.25 mg QD × 28 days | 50 mg QD × 8 days | 17-Deacetyl norgestimate | ↑ 6% | ↑ 2%
QD = once daily; INR = international normalized ratio; ↑ = increase; ↓ = decrease

13 NONCLINICAL TOXICOLOGY

13.1 Carcinogenesis, Mutagenesis, Impairment of Fertility

In a 2-year dietary carcinogenicity study in mice, lomitapide was administered at doses of 0.3, 1.5, 7.5, 15, or 45 mg/kg/day. There were statistically significant increases in the incidences of liver adenomas and carcinomas in males at doses ≥1.5 mg/kg/day (≥2-times the MRHD at 60 mg based on AUC) and in females at ≥7.5 mg/kg/day (≥10-times the human exposure at 60 mg based on AUC). Incidences of small intestinal carcinomas in males and combined adenomas and carcinomas in females were significantly increased at doses ≥15 mg/kg/day (≥23-times the human exposure at 60 mg based on AUC).

In a 2-year carcinogenicity study in rats, lomitapide was administered by oral gavage for up to 99 weeks at doses of 0.25, 1.7, or 7.5 mg/kg/day in males and 0.03, 0.35, or 2.0 mg/kg/day in females. While the design of the study was suboptimal, there were no statistically significant drug-related increases in tumor incidences at exposures up to 6-times (males) and 8-times (females) higher than human exposure at the MRHD based on AUC.

Lomitapide did not exhibit genotoxic potential in a battery of studies, including the in vitro Bacterial Reverse Mutation (Ames) assay, an in vitro cytogenetics assay using primary human lymphocytes, and an oral micronucleus study in rats.

Lomitapide had no effect on fertility in rats at doses up to 5 mg/kg/day at systemic exposures estimated to be 4-times (females) and 5-times (males) higher than in humans at 60 mg based on AUC.

14 CLINICAL STUDIES

The safety and effectiveness of JUXTAPID as an adjunct to a low-fat diet and other lipid-lowering treatments, including LDL apheresis where available, were evaluated in a multinational, single-arm, open-label, 78-week trial involving 29 adults with HoFH. A diagnosis of HoFH was defined by the presence of at least one of the following clinical criteria: (1) documented functional mutation(s) in both LDL receptor alleles or alleles known to affect LDL receptor functionality, or (2) skin fibroblast LDL receptor activity <20% normal, or (3) untreated TC >500 mg/dL and TG <300 mg/dL and both parents with documented untreated TC >250 mg/dL.

Among the 29 patients enrolled, the mean age was 30.7 years (range, 18 to 55 years), 16 (55%) were men, and the majority (86%) were Caucasian. The mean body mass index (BMI) was 25.8 kg/m^2, with four patients meeting BMI criteria for obesity; one patient had type 2 diabetes. Concomitant lipid-lowering treatments at baseline included one or more of the following: statins (93%), ezetimibe (76%), nicotinic acid (10%), bile acid sequestrant (3%), and fibrate (3%); 18 (62%) were receiving apheresis.

After a six-week run-in period to stabilize lipid-lowering treatments, including the establishment of an LDL apheresis schedule if applicable, JUXTAPID was initiated at 5 mg daily and titrated to daily doses of 10 mg, 20 mg, 40 mg, and 60 mg at weeks 2, 6, 10, and 14, respectively, based on tolerability and acceptable levels of transaminases. Patients were instructed to maintain a low-fat diet (<20% calories from fat) and to take dietary supplements that provided approximately 400 international units vitamin E, 210 mg alpha-linolenic acid (ALA), 200 mg linoleic acid, 110 mg eicosapentaenoic acid (EPA), and 80 mg docosahexaenoic acid (DHA) per day. After efficacy was assessed at Week 26, patients remained on JUXTAPID for an additional 52 weeks to assess long-term safety. During this safety phase, the dose of JUXTAPID was not increased above each patient's maximum tolerated dose established during the efficacy phase, but changes to concomitant lipid-lowering treatments were allowed.

Twenty-three (79%) patients completed the efficacy endpoint at Week 26, all of whom went on to complete 78 weeks of treatment. Adverse events contributed to premature discontinuation for five patients [see Adverse Reactions (6.1)]. The maximum tolerated doses during the efficacy period were 5 mg (10%), 10 mg (7%), 20 mg (21%), 40 mg (24%), and 60 mg (34%).

The primary efficacy endpoint was percent change in LDL-C from baseline to Week 26. At Week 26, the mean and median percent changes in LDL-C from baseline were -40% (paired t-test p<0.001) and -50%, respectively, based on the intent-to-treat population with last observation carried forward (LOCF) for patients who discontinued prematurely. The mean percent change in LDL-C from baseline through Week 26 is shown in Figure 1 for the 23 patients who completed the efficacy period.

Figure 1: Mean Percent Change in LDL-C from Baseline (Week 26 Completers)

Error bars represent 95% confidence intervals of the mean.

Changes in lipids and lipoproteins through the efficacy endpoint at Week 26 are presented in Table 8.

Table 8: Absolute Values and Percent Changes from Baseline in Lipids and Lipoproteins
PARAMETER | BASELINE | WEEK 26/LOCF (N=29)
PARAMETER | Mean (SD) | Mean (SD) | Mean % Change
LDL-C, direct (mg/dL) | 336 (114) | 190 (104) | -40 [Statistically significant compared with baseline based on the pre-specified gatekeeping method for controlling Type I error among the primary and key secondary endpoints.]
TC (mg/dL) | 430 (135) | 258 (118) | -36
apo B (mg/dL) | 259 (80) | 148 (74) | -39
Non-HDL-C (mg/dL) | 386 (132) | 217 (113) | -40
VLDL-C (mg/dL) | 21 (10) | 13 (9) | -29
TG (mg/dL) [Median values with interquartile range and median % change presented for TG.] | 92 [72, 128] | 57 [36, 78] | -45
HDL-C (mg/dL) | 44 (11) | 41 (13) | -7

After Week 26, during the safety phase of the study, adjustments to concomitant lipid-lowering treatments were allowed. For the study population overall, average reductions in LDL-C, TC, apo B, and non-HDL-C were sustained during chronic therapy.

16 HOW SUPPLIED / STORAGE AND HANDLING

5 mg capsules:

Orange/orange hard gelatin capsule printed with black ink "A733" and "5 mg"

Bottles of 28 | NDC 76431-105-01

10 mg capsules:

Orange/white hard gelatin capsule printed with black ink "A733" and "10 mg"

Bottles of 28 | NDC 76431-110-01

20 mg capsules:

White/white hard gelatin capsule printed with black ink "A733" and "20 mg"

Bottles of 28 | NDC 76431-120-01

30 mg capsules:

Orange/yellow hard gelatin capsule printed with black ink "A733" and "30 mg"

Bottles of 28 | NDC 76431-130-01

STORAGE AND HANDLING

Storage: Store at 20°C to 25°C (68°F to 77°F); excursions permitted between 15°C and 30°C (between 59°F and 86°F). Brief exposure to temperatures up to 40°C (104°F) may be tolerated provided the mean kinetic temperature does not exceed 25°C (77°F); however, such exposure should be minimized. Keep container tightly closed and protect from moisture.

17 PATIENT COUNSELING INFORMATION

See FDA-approved labeling (Medication Guide)

Patients should be informed that a registry for patients taking JUXTAPID has been established in order to monitor and evaluate the long-term effects of JUXTAPID. Patients are encouraged to participate in the registry and should be informed that their participation is voluntary. For information regarding the registry program visit www.JUXTAPID.com or call 1-877-902-4099.

Advise patients of the following:

Risk of Hepatotoxicity [see Warnings and Precautions (5.1)]

- JUXTAPID can cause both elevations in transaminases and hepatic steatosis. Discuss with the patient the importance of monitoring of liver-related tests before taking JUXTAPID, prior to each dose escalation, and periodically thereafter.
- Patients should be advised of the potential for increased risk of liver injury if alcohol is consumed while taking JUXTAPID. It is recommended that patients taking JUXTAPID limit consumption to not more than one alcoholic drink per day.
- JUXTAPID is commonly associated with nausea, vomiting, and abdominal pain. Advise patients to promptly report these symptoms if they increase in severity, persist, or change in the character, as they might reflect liver injury. Patients should also report any other symptoms of possible liver injury, including fever, jaundice, lethargy, or flu-like symptoms.

JUXTAPID REMS Program [see Warnings and Precautions (5.2)]

- JUXTAPID is only available through a restricted program called JUXTAPID REMS Program and therefore, JUXTAPID is only available from certified pharmacies that are enrolled in the program.

Embryofetal Toxicity [see Warnings and Precautions (5.3), Drug Interactions (7.2), Use in Specific Populations (8.1, 8.3)]

- JUXTAPID is contraindicated in pregnancy since it may cause fetal harm. Advise females who become pregnant to discontinue JUXTAPID and inform their healthcare provider of a known or suspected pregnancy.
- Advise females of reproductive potential to use effective contraception during treatment with JUXTAPID and for two weeks after the final dose.
- Advise patients who are taking oral contraceptives and experience vomiting or diarrhea while taking JUXTAPID to use an effective alternative contraceptive method until 7 days after resolution of symptoms.

Lactation [see Use in Specific Populations (8.2)]

Advise females not to breastfeed during treatment with JUXTAPID.

Dietary Supplements [see Warnings and Precautions (5.4)]

- Discuss with the patient the importance of taking daily supplements that contain 400 international units vitamin E and at least 200 mg linoleic acid, 210 mg alpha-linolenic acid (ALA), 110 mg eicosapentaenoic acid (EPA), and 80 mg docosahexaenoic acid (DHA).

Gastrointestinal Adverse Reactions [see Warnings and Precautions (5.5)]

- Inform the patient that gastrointestinal adverse reactions are common with JUXTAPID. These include, but are not limited to, diarrhea, nausea/vomiting, abdominal pain/discomfort, flatulence, and constipation. Strict adherence to a low-fat diet (<20% of total calories from fat) may reduce these reactions.
- Instruct the patient to stop JUXTAPID and contact their healthcare provider if severe diarrhea occurs or if they experience symptoms of volume depletion such as lightheadedness, decreased urine output, or tiredness.
- Tell the patient that taking JUXTAPID with food may adversely impact gastrointestinal tolerability; therefore, they should take JUXTAPID at least 2 hours after the evening meal, swallowing each capsule whole.
- Absorption of oral medications may be affected in patients who develop diarrhea or vomiting. For example, hormone absorption from oral contraceptives may be incomplete, warranting the use of additional contraceptive methods. Patients who develop these symptoms should seek advice from their healthcare provider.

Drug Interactions [see Warnings and Precautions (5.6) and Drug Interactions (7)]

- Tell the patient to omit grapefruit juice from his/her diet while on JUXTAPID.
- Because multiple drug-drug interactions have been described with JUXTAPID, advise the patient to tell their healthcare provider(s) about all medications, nutritional supplements, and vitamins that they are taking or may be taking while taking JUXTAPID.

Missed Doses

- If a dose of JUXTAPID is missed, the normal dose should be taken at the usual time the next day. If dosing is interrupted for more than a week, tell the patient to contact their healthcare provider before restarting treatment.

AMRYT
PHARMA

Medication Guide
JUXTAPID® (JUKS-tuh-pid)
(lomitapide)
capsules

What is the most important information I should know about JUXTAPID?

- JUXTAPID is available only through certified pharmacies that are enrolled in the JUXTAPID REMS Program. Your doctor must be enrolled in the program in order for you to be prescribed JUXTAPID.
- There is a registry that collects information about the effects of taking JUXTAPID over time. Ask your doctor for more information about this registry or visit www.JUXTAPID.com or call 1-877-902-4099.

JUXTAPID may cause serious side effects including:
1. Liver problems. JUXTAPID can cause liver problems such as increased liver enzymes or increased fat in the liver.

- Your doctor should do blood tests to check your liver before you start JUXTAPID, if your dose is increased, and while you take JUXTAPID. If your tests show some liver problems, your doctor may adjust your dose of JUXTAPID or stop it altogether.
- Tell your doctor if you have had liver problems, including liver problems while taking other medicines.
- JUXTAPID may cause nausea, vomiting and stomach pain, especially if you do not eat a low-fat diet. These side effects can also be symptoms of liver problems.
- Tell your doctor right away if you have any of these symptoms of liver problems while taking JUXTAPID:
  - Nausea, vomiting, or stomach pain that gets worse, does not go away, or changes
  - fever
  - flu-like symptoms
  - yellowing of your eyes or skin
  - you are more tired than usual
- Drinking alcohol may increase your chance of having liver problems or make your liver problems worse. You should not have more than 1 alcoholic drink each day while taking JUXTAPID.

2. Harm to your unborn baby. JUXTAPID may cause harm to your unborn baby.

- If you are pregnant, think you may be pregnant, or are planning to become pregnant, do not take JUXTAPID.
- If you are a female who can get pregnant, you should have a pregnancy test before you start taking JUXTAPID. Your pregnancy test must be negative for you to get JUXTAPID.
  - Do not have sex while taking JUXTAPID unless you are using effective birth control.
  - Talk with your doctor or nurse to find the best method of birth control for you.
  - Birth control pills may not work as well if you have diarrhea or vomiting.
  - If you start taking birth control pills while you are taking JUXTAPID, tell your doctor. Your doctor might need to change your dose of JUXTAPID.
- If you become pregnant while taking JUXTAPID, stop taking JUXTAPID and call your doctor right away.
  - Pregnancy Exposure Registry: There is a pregnancy exposure registry that monitors outcomes in women exposed to JUXTAPID during pregnancy. If you become pregnant while taking JUXTAPID, call 1-877-902-4099 or visit www.JUXTAPID.com for more information about the JUXTAPID pregnancy exposure registry.

What is JUXTAPID?

JUXTAPID is a prescription medicine used along with diet and other lipid-lowering treatments, including low-density lipoprotein (LDL) apheresis where available, in people with homozygous familial hypercholesterolemia (HoFH) to reduce:

- LDL ("bad") cholesterol
- total cholesterol
- a protein that carries "bad" cholesterol in the blood (apolipoprotein B)
- non-high-density lipoprotein cholesterol (non-HDL-C)

It is not known if JUXTAPID can decrease problems from high cholesterol, such as heart attack, stroke, death or other health problems.

It is not known if JUXTAPID is safe and effective in people with high cholesterol who do not have HoFH, including those with heterozygous familial hypercholesterolemia (HeFH).

JUXTAPID should not be taken with certain medicines or food. You should not drink grapefruit juice. Ask your doctor or pharmacist to make sure you can take JUXTAPID with your other medicines, and tell your doctor about any new medicines you might take even for only a short time.

It is not known if JUXTAPID is safe and effective in people with kidney problems including people with end-stage kidney disease who are not on dialysis.

It is not known if JUXTAPID is safe and effective when used in children under the age of 18.

Who should not take JUXTAPID?

Do not take JUXTAPID if you:

- are pregnant, think you may be pregnant, or are planning to become pregnant. See "What is the most important information I should know about JUXTAPID?"
- take medicines that affect how the body breaks down JUXTAPID (that is, strong or moderate CYP3A4 inhibitors). Check with your doctor and/or pharmacist to see if you are taking any of these medications. These may include certain medications intended to treat bacterial, fungal or viral infections, and medications to treat depression, high blood pressure, or angina.
- drink grapefruit juice
- have moderate or severe liver problems or active liver disease, including people who have unexplained abnormal liver tests.

What should I tell my doctor before taking JUXTAPID?

Before you take JUXTAPID, tell your doctor if you:

- have liver problems
- have kidney problems
- have intestine or bowel problems
- drink alcohol
- are breastfeeding or plan to breastfeed. It is not known if JUXTAPID passes into your breast milk. You and your doctor should decide if you will take JUXTAPID or breastfeed. You should not do both.

Tell your doctor about all the medicines you take, including prescription and over-the-counter medicines, vitamins, and herbal supplements.

Before starting a new medicine while taking JUXTAPID, even if you will only be taking it for a short time, ask your doctor or pharmacist if it is safe to take with JUXTAPID.

JUXTAPID may affect the way other medicines work, and other medicines may affect how JUXTAPID works.

Certain medicines can affect how your liver breaks down other medicines.

Especially tell your doctor if you take:

- a blood thinner called warfarin
- medicines for high cholesterol, including statins such as atorvastatin or simvastatin, and resins such as colesevelam or cholestyramine
- medicines for bacteria, fungus, or viral infection (including HIV and hepatitis C)
- medicines for depression, high blood pressure, or angina
- birth control pills

Know the medicines you take. Keep a list of them to show your doctor and pharmacist when you get a new medicine.

How should I take JUXTAPID?

- Take JUXTAPID exactly as your doctor tells you to take it.
- Your doctor will tell you how much JUXTAPID to take and when to take it.
- Your doctor may change your dose of JUXTAPID if needed.
- Do not change your JUXTAPID dose yourself.
- Take JUXTAPID 1 time each day at least 2 hours after your evening meal.
- Take JUXTAPID with water.
- You should not take JUXTAPID with food. Taking JUXTAPID with food may cause stomach problems.
- Take JUXTAPID capsules whole. Do not open, crush, dissolve, or chew capsules before swallowing. If you cannot swallow JUXTAPID capsules whole, tell your doctor. You may need a different medicine.
- If you take a medicine that lowers cholesterol by binding bile acids, such as colesevelam or cholestyramine, take it at least 4 hours before or 4 hours after you take JUXTAPID. Ask your doctor if you are not sure if you take these medicines.
- To help lower the chance of stomach problems, stay on a low-fat diet. Ask your doctor about talking to a dietician to learn what you should eat while taking JUXTAPID. JUXTAPID makes it harder for some nutrients to get into your body. Take Vitamin E and fatty acids each day while you take JUXTAPID. Ask your doctor, nurse, or dietician how to add them to your diet.
- If you take too much JUXTAPID, call your doctor right away.
- Do not stop JUXTAPID unless your doctor tells you to stop it.
- If you miss a dose of JUXTAPID, take your usual dose the next day at the usual time. If you stop taking JUXTAPID for more than a week, talk to your doctor before restarting treatment.

What are the possible side effects of JUXTAPID?

JUXTAPID can cause serious side effects, including:

- See "What is the most important information I should know about JUXTAPID?"
- problems absorbing certain nutrients. JUXTAPID may decrease your ability to absorb fat-soluble nutrients such as Vitamin E and fatty acids. You should take supplements each day that contain fat-soluble vitamins. People with bowel or pancreas problems may have an increased chance of not being able to absorb these nutrients. See "How should I take JUXTAPID?"
- gastrointestinal symptoms. Diarrhea, nausea, vomiting, and stomach pain or discomfort are very common when taking JUXTAPID. Strictly following a low-fat diet may help lower the chance of having these symptoms. Stop taking Juxtapid and tell your doctor if you have severe diarrhea, especially if you also have lightheadedness, decreased urine output, or tiredness.
- increased levels of certain blood thinners. JUXTAPID can increase the level of the blood thinner, warfarin. If you take warfarin, your doctor should check your blood clotting times frequently, especially after your dose of JUXTAPID changes.
- liver problems caused by certain drugs. Certain medicines can cause liver problems, including isotretinoin, acetaminophen, methotrexate, tetracyclines, and tamoxifen. If you take these medicines with JUXTAPID your doctor may do blood tests more often to check your liver.

The most common side effects of JUXTAPID include:

- diarrhea
- nausea
- vomiting
- indigestion
- stomach cramping/pain

Tell your doctor if you have any side effect that bothers you or that does not go away.

These are not all the possible side effects of JUXTAPID. For more information, ask your doctor or pharmacist.

Call your doctor for medical advice about side effects. You may report side effects to FDA at 1-800-FDA-1088.

How should I store JUXTAPID?

- Store JUXTAPID at room temperature, between 68°F and 77F° (20°C and 25°C).
- Keep JUXTAPID in a tightly closed container.
- Keep JUXTAPID capsules dry.
- Safely throw away medicine that is out of date or no longer needed.

Keep JUXTAPID and all medicines out of the reach of children.

General information about the safe and effective use of JUXTAPID.

Medicines are sometimes prescribed for purposes other than those listed in a Medication Guide. Do not use JUXTAPID for a condition for which it was not prescribed. Do not give JUXTAPID to other people, even if they have the same symptoms you have. It may harm them.

This Medication Guide summarizes the most important information about JUXTAPID. If you would like more information, talk with your doctor. You can ask your pharmacist or doctor for information about JUXTAPID that is written for healthcare professionals.

For more information, go to www.JUXTAPID.com or call 1-85-JUXTAPID (1-855-898-2743).

What are the ingredients in JUXTAPID?

Active ingredient: lomitapide mesylate

Inactive ingredients: pregelatinized starch, sodium starch glycolate, microcrystalline cellulose, lactose monohydrate, silicon dioxide, magnesium stearate

Capsule shell: The capsule shells of all strengths contain gelatin and titanium dioxide; the 5 mg, 10 mg and 30 mg capsules also contain red iron oxide; and the 30 mg capsules also contain yellow iron oxide. The imprinting ink contains shellac, black iron oxide, and propylene glycol.

AMRYT
PHARMA

JUXTAPID is a registered trademark and the property of the Amryt Pharma Group ©2020 All rights reserved.

Manufactured for: Amryt Pharmaceuticals DAC, Dublin, Ireland

This Medication Guide has been approved by the U.S. Food and Drug Administration.

05/2016
PN 4007-16

PRINCIPAL DISPLAY PANEL - 5 mg Capsule Bottle Label

NDC 76431-105-01

28 capsules

Juxtapid®
(lomitapide) capsules

5 mg

AMRYT
PHARMA

PRINCIPAL DISPLAY PANEL - 5 mg Capsule Bottle Carton

NDC 76431-105-01
Rx Only

28 capsules

Juxtapid®
(lomitapide) capsules

5 mg

Attention Pharmacist:
Dispense the accompanying
Medication Guide to each patient.

AMRYT
PHARMA

PRINCIPAL DISPLAY PANEL - 10 mg Capsule Bottle Label

NDC 76431-110-01

28 capsules

Juxtapid®
(lomitapide) capsules

10 mg

AMRYT
PHARMA

PRINCIPAL DISPLAY PANEL - 10 mg Capsule Bottle Carton

NDC 76431-110-01
Rx Only

28 capsules

Juxtapid®
(lomitapide) capsules

10 mg

Attention Pharmacist:
Dispense the accompanying
Medication Guide to each patient.

AMRYT
PHARMA

PRINCIPAL DISPLAY PANEL - 20 mg Capsule Bottle Label

NDC 76431-120-01

28 capsules

Juxtapid®
(lomitapide) capsules

20 mg

AMRYT
PHARMA

PRINCIPAL DISPLAY PANEL - 20 mg Capsule Bottle Carton

NDC 76431-120-01
Rx Only

28 capsules

Juxtapid®
(lomitapide) capsules

20 mg

Attention Pharmacist:
Dispense the accompanying
Medication Guide to each patient.

AMRYT
PHARMA

PRINCIPAL DISPLAY PANEL - 30 mg Capsule Bottle Label

NDC 76431-130-01

28 capsules

Juxtapid®
(lomitapide) capsules

30 mg

AMRYT
PHARMA

PRINCIPAL DISPLAY PANEL - 30 mg Capsule Bottle Carton

NDC 76431-130-01
Rx Only

28 capsules

Juxtapid®
(lomitapide) capsules

30 mg

Attention Pharmacist:
Dispense the accompanying
Medication Guide to each patient.

AMRYT
PHARMA